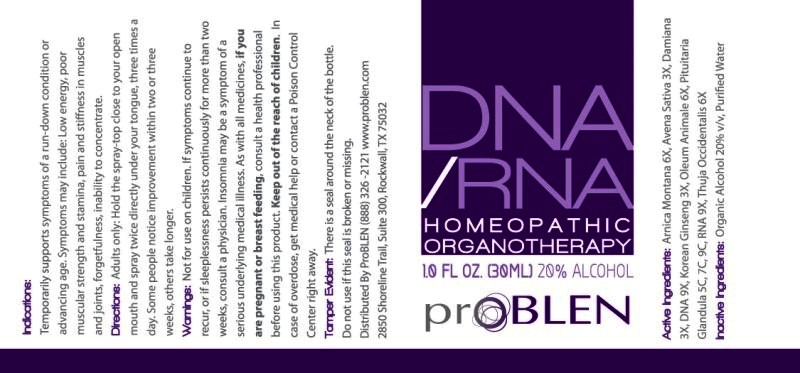 DRUG LABEL: DNA RNA
NDC: 43853-0014 | Form: SPRAY
Manufacturer: ProBLEN
Category: homeopathic | Type: HUMAN OTC DRUG LABEL
Date: 20161123

ACTIVE INGREDIENTS: ARNICA MONTANA 6 [hp_X]/1 mL; AVENA SATIVA FLOWERING TOP 3 [hp_X]/1 mL; TURNERA DIFFUSA LEAFY TWIG 3 [hp_X]/1 mL; HERRING SPERM DNA 9 [hp_X]/1 mL; SUS SCROFA PITUITARY GLAND 5 [hp_C]/1 mL; CERVUS ELAPHUS HORN OIL 6 [hp_X]/1 mL; ASIAN GINSENG 3 [hp_X]/1 mL; SACCHAROMYCES CEREVISIAE RNA 9 [hp_X]/1 mL; THUJA OCCIDENTALIS LEAFY TWIG 6 [hp_X]/1 mL
INACTIVE INGREDIENTS: WATER; ALCOHOL

Drug Facts:

ACTIVE INGREDIENTS:

Arnica Montana 6X, Avena Sativa 3X, Damiana 3X, DNA 9X, Hypophysis Suis 5C, 7C, 9C, Oleum Animale 6X, Panax Ginseng 3X, RNA 9X, Thuja Occidentalis 6X

INDICATIONS:

Temporarily supports symptoms of a run-down condition or advancing age. Symptoms may include: Low energy, poor muscular strength and stamina, pain and stiffness in muscles and joints, forgetfulness, inability to concentrate.

WARNINGS:

Not for use on children.

If symptoms continue to recur, or if sleeplessness persists continuously for more than two weeks, consult a physician. Insomnia may be a symptom of a serious underlying medical illness.

As with all medicines, if you are pregnant or breast feeding, consult a health professional before using this product.

Keep out of the reach of children. In case of overdose, get medical help or contact a Poison Control Center right away.

Tamper Evident: There is a seal around the neck of the bottle. Do not use if this seal is broken or missing.

KEEP OUT OF REACH OF CHILDREN:

Keep out of the reach of children. In case of overdose, get medical help or contact a Poison Control Center right away.

DIRECTIONS:

Adults only: Hold the spray-top close to your open mouth and spray twice directly under your tongue, three times a day. Some people notice improvement within two or three weeks, others take longer.

INDICATIONS:

Temporarily supports symptoms of a run-down condition or advancing age. Symptoms may include: Low energy, poor muscular strength and stamina, pain and stiffness in muscles and joints, forgetfulness, inability to concentrate.

INACTIVE INGREDIENTS:-

Organic Alcohol 20% v/v, Purified Water

QUESTIONS:

Distributed By ProBLEN (888) 326-2121 www.problen.com
2850 Shoreline Trail, Suite 300, Rockwall, TX 75032

PACKAGE LABEL DISPLAY:

DNA / RNA

HOMEOPATHIC ORGANOTHERAPY

1.0 FL. OZ. (30 ML)

proBLEN